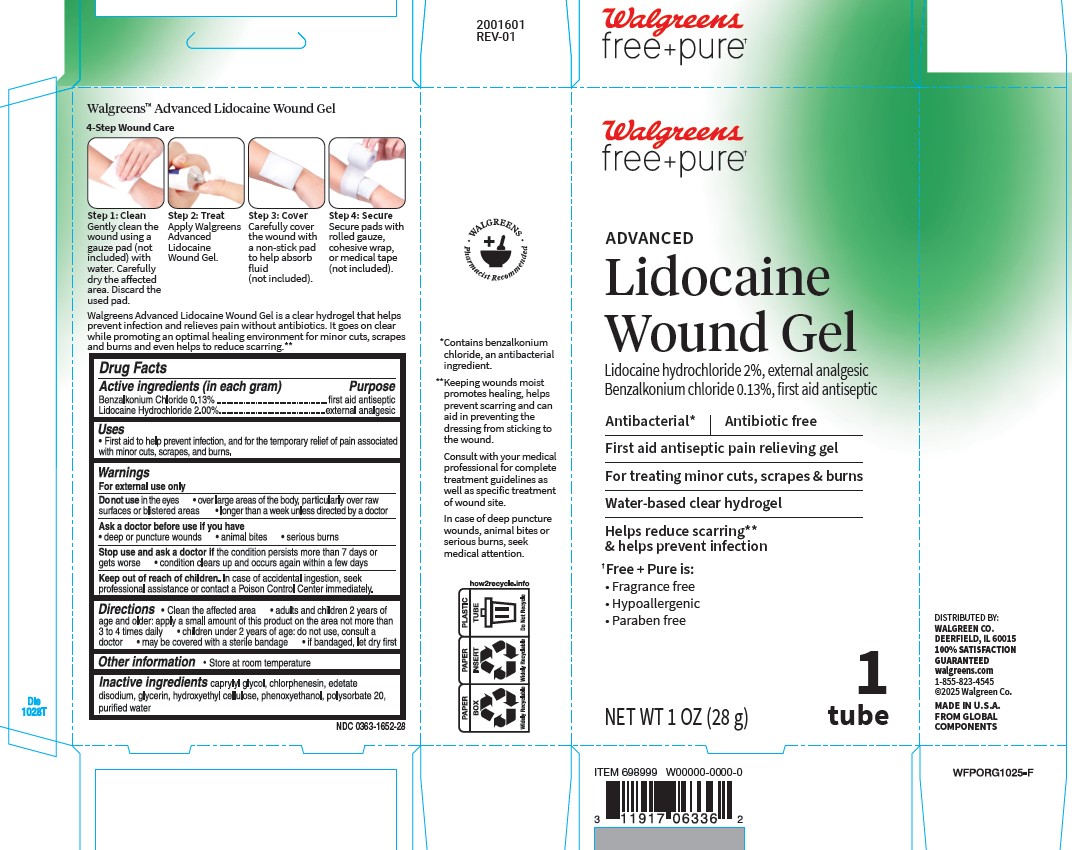 DRUG LABEL: Antibacterial Lidocaine Wound Gel
NDC: 0363-1652 | Form: GEL
Manufacturer: WALGREENS
Category: otc | Type: HUMAN OTC DRUG LABEL
Date: 20251014

ACTIVE INGREDIENTS: LIDOCAINE HYDROCHLORIDE 2 g/100 mL; BENZALKONIUM CHLORIDE 0.13 g/100 mL
INACTIVE INGREDIENTS: WATER; HYDROXYETHYL CELLULOSE, UNSPECIFIED; CAPRYLYL GLYCOL; EDETATE DISODIUM; GLYCERIN; CHLORPHENESIN; POLYSORBATE 20; PHENOXYETHANOL

Advanced Lidocaine Wound Gel

Active ingredient (in each gram)

Benzalkonium Chloride 0.13%
Lidocaine Hydrochloride 2.00%

Purpose

first aid antiseptic
external analgesic

Uses

- First aid to help prevent infection, and for the temporary relief of pain associated with minor cuts, scrapes and burns

Warnings

For external use only

Do not use

- in the eyes
- over large areas of the body, particularly over raw surfaces or blistered areas
- longer than a week unless directed by a doctor

Ask a doctor before use if you have

- deep or puncture wounds
- animal bites
- serious burns

Stop use and ask a doctor if

- the condition persists more than 7 days or gets worse
- condition clears up and occurs again within a few days

Keep out of reach of children.

In case of accidental ingestion, seek professional assistance or contact a Poison Control Center immediately.

Directions

- clean the affected area
- adults and children 2 years of age and older: apply to affected area not more than 3 to 4 times daily
- children under 2 years of age: consult a doctor
- may be covered with a sterile bandage
- if bandaged, let dry first

Other information

Store at room temperature

Inactive ingredients

caprylyl glycol, chlorphenesin, edetate disodium, glycerin, hydroxyethyl cellulose, phenoxyethanol, polysorbate 20, purified water

Principal Display Panel

Walgreens

Free+pure

ADVANCED

Lidocaine Wound Gel

Lidocaine Hydrochloride 2%, external analgesic

Benzalkonium Chloride 0.13%, first aid antiseptic

Antibacterial* I Antibiotic free

First aid antiseptic pain relieving gel

For treating minor cuts, scrapes and burns

Water-based clear hydrogel

Helps reduce scarring** and helps prevent infection

Free+Pure is:

- Fragrance free
- Hypoallergenic
- Paraben free